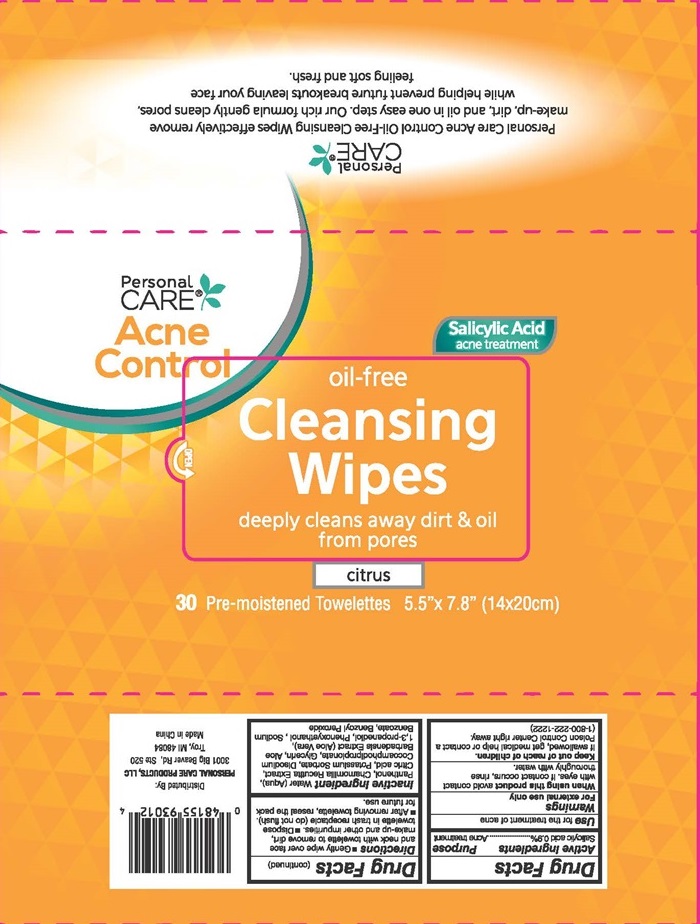 DRUG LABEL: Acne Control oil-free Cleansing
NDC: 29500-9082 | Form: LIQUID
Manufacturer: Personal Care Products, LLC
Category: otc | Type: HUMAN OTC DRUG LABEL
Date: 20151013

ACTIVE INGREDIENTS: SALICYLIC ACID 29.2 mg/1 1
INACTIVE INGREDIENTS: WATER; PANTHENOL; MATRICARIA RECUTITA; CITRIC ACID MONOHYDRATE; POTASSIUM SORBATE; DISODIUM COCOAMPHODIPROPIONATE; GLYCERIN; ALOE VERA LEAF; PROPANEDIOL; PHENOXYETHANOL; SODIUM BENZOATE; BENZOYL PEROXIDE

Drug Facts Active ingredients

Salicylic acid 0.9%

Purpose

Acne treatment

Keep out of reach of children.

If swallowed, get medical help or contact a Poison Control Center right away.

Use

for the treatment of acne

Warnings

For external use only

Directions

- Gently wipe over face and neck with towelette to remove dirt, make-up and other impurities.
- Dispose towelette in trash receptacle (do not flush).
- After removing towelette, reseal the pack for future use.

Inactive Ingredients

Water (Aqua), Panthenol, Chamomlla Recutta Extract, Citric acid, Potassium Sorbate, Disodium Cocoamphodlproplonate, Glycerin, Aloe Barbadensis Extract (Aloe Vera), 1,3-propanedlol, Phenoxyethanol, Sodium Benzoate, Benzoyl Peroxide

Personal CARE® Acne Control oil-free Cleansing Wipes

Personal CARE®

Acne Control

Salicylic Acid acne treatment

oil-free

Cleansing Wipes

deeply cleans away dirt & oil from pores

citrus

30 pre-moistened Towelettes 5.5"x7.8" (14x20cm)

Personal CARE®

Personal Care Acne Control Oli-Free Cleansing Wipes effectively remove make-up, dirt, and oil in one easy step. Our rich formula gently cleans pores, while helping preveny future breakouts leaving your face feeling soft and fresh.

Distributed By:

PERSONAL CARE PRODUCTS, LLC

3011 Big BeaverRd. Ste 520

Troy, MI 48084

Made in China